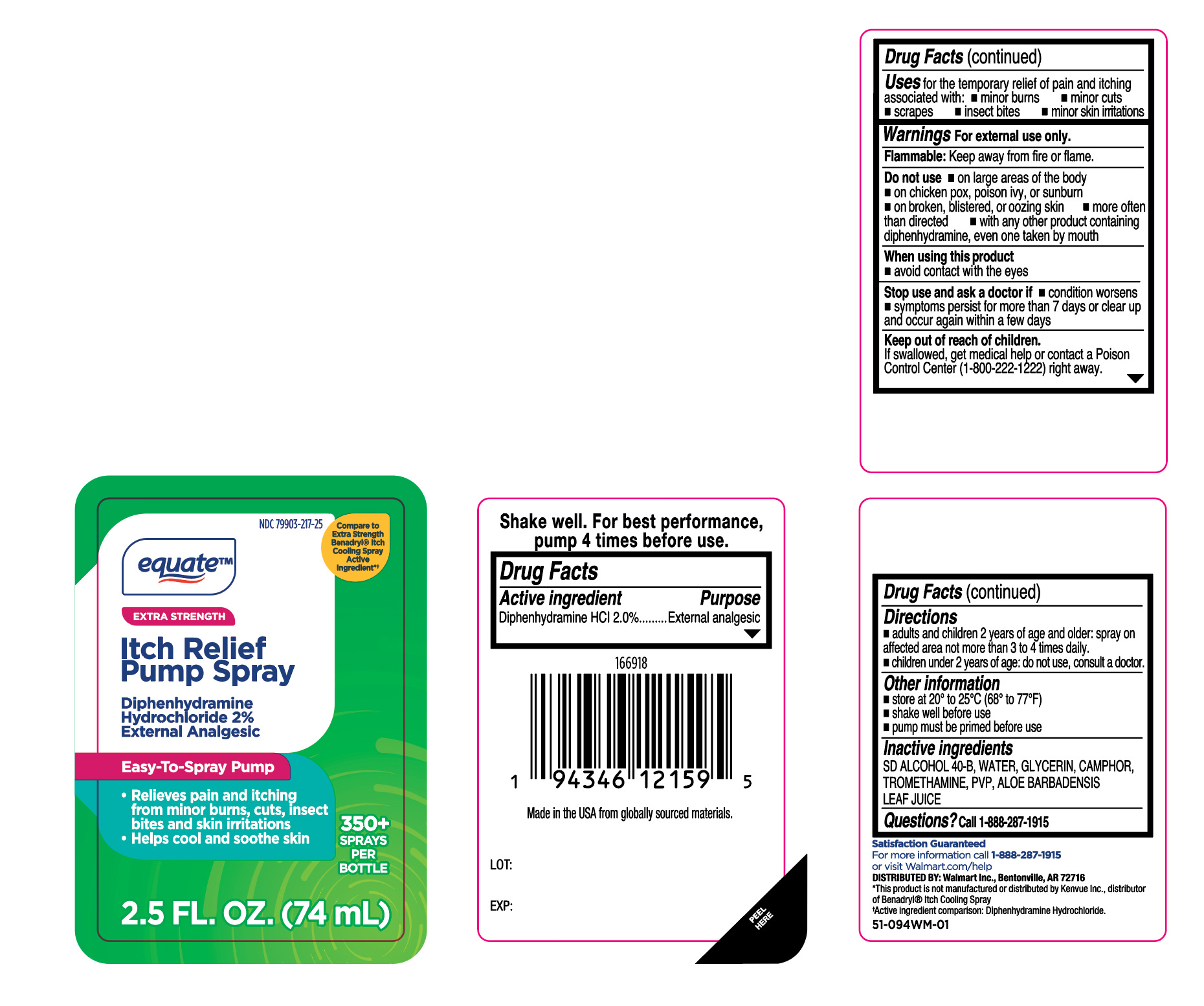 DRUG LABEL: Itch Relief
NDC: 79903-217 | Form: SPRAY
Manufacturer: Wal-Mart Stores, Inc.
Category: otc | Type: HUMAN OTC DRUG LABEL
Date: 20260127

ACTIVE INGREDIENTS: DIPHENHYDRAMINE HYDROCHLORIDE 20 mg/1 mL
INACTIVE INGREDIENTS: CAMPHOR (NATURAL); POVIDONE; TROMETHAMINE; GLYCERIN; WATER; ALCOHOL; ALOE VERA LEAF

Equate Itch Relief Pump Spray

Active ingredients

Diphenhydramine HCl 2.0%,

Purpose

External analgesic

Uses

for the temporary relief of pain and itching associated with:

- minor burns
- minor cuts
- scrapes
- insect bites
- minor skin irritations

Warnings

For external use only.

Flammable:

Keep away from fire or flame.

Do not use

- on large areas of the body
- on chicken pox, poison ivy, or sunburn
- on broken, blistered, or oozing skin
- more often than directed
- with any other product containing diphenhydramine, even one taken by mouth

When using this product

- avoid contact with the eyes

Stop use and ask doctor if

- conditions worsens
- symptoms persist for more than 7 days or clear up and occur again within a few days

Keep out of reach of children.

If swallowed, get medical help or contact a Poison Control Center (1-800-222-1222) right away.

Directions

- adults and children 2 years of age and older: spray on affected area not more than 3 to 4 times daily
- children under 2 years of age: do not use, consult a doctor

Other information

- store at 20° to 25°C (68° to 77°F)
- shake well before use
- pump must be primed before use

Inactive ingredients

SD ALCOHOL 40-B, WATER, GLYCERIN, CAMPHOR, TROMETHAMINE, PVP, ALOE BARBADENSIS LEAF JUICE

Questions?

1-888-287-1915

Principal Display Panel

Equate

Extra Strength

Itch Relief

Pump Spray

Diphenhydramine

Hydrochloride 2%

External Analgesic

Easy-To-Spray Pump

- Relieves pain and itching from minor burns, cuts, insect bites, and skin irritations
- Helps cool and soothe skin

2.5 FL. OZ. (74mL)